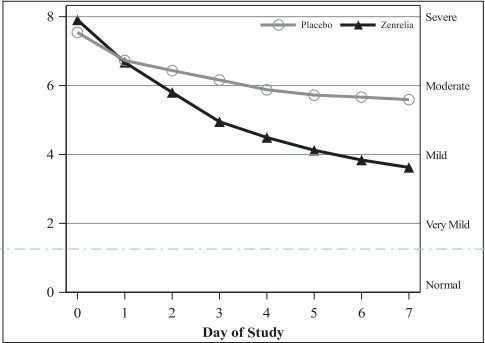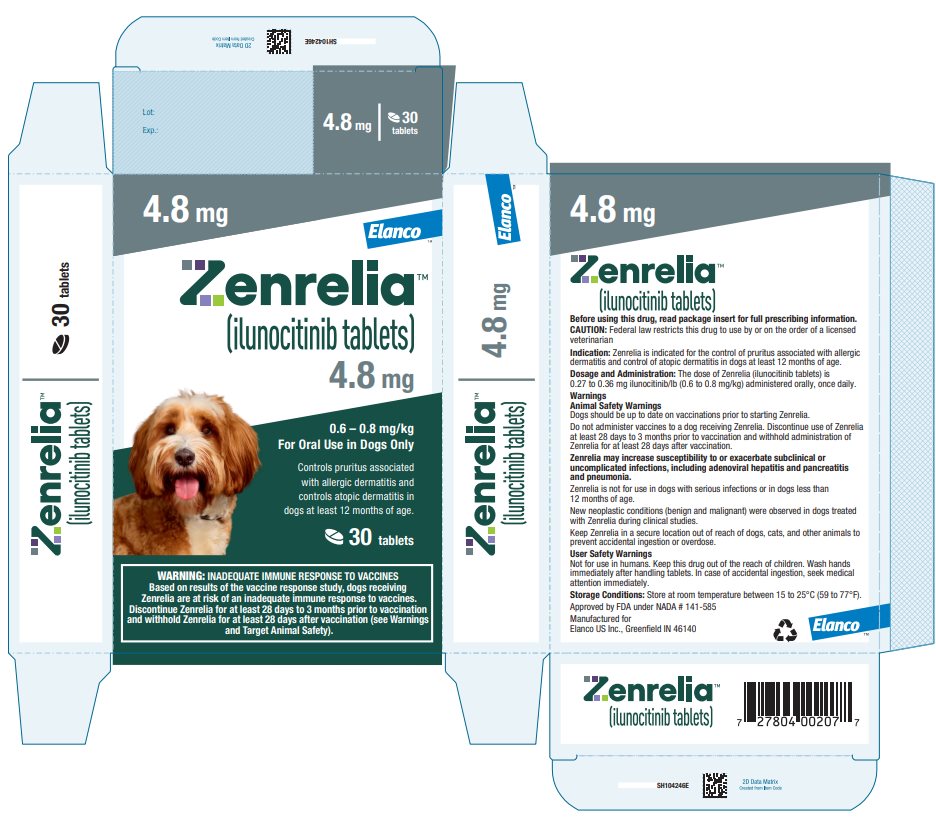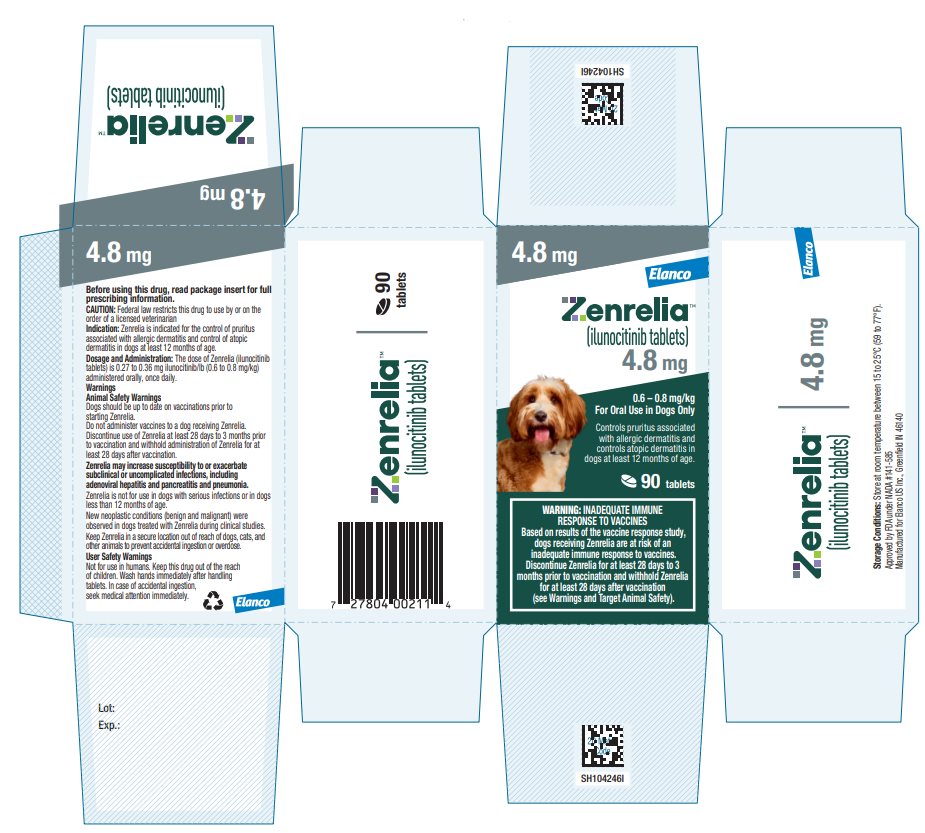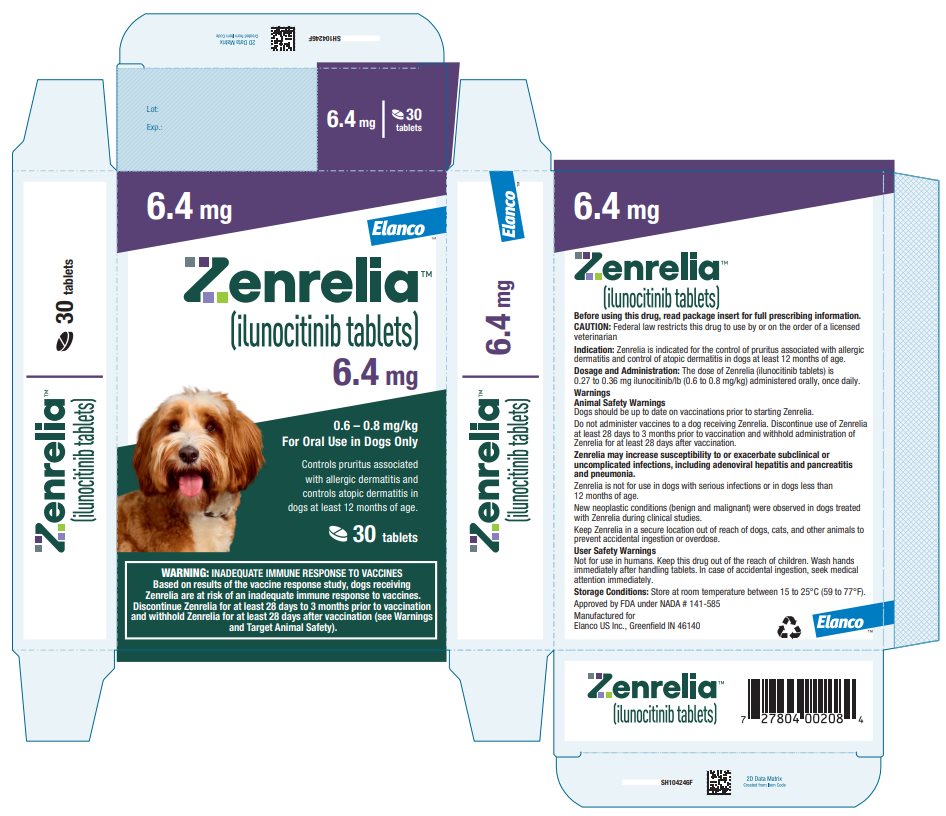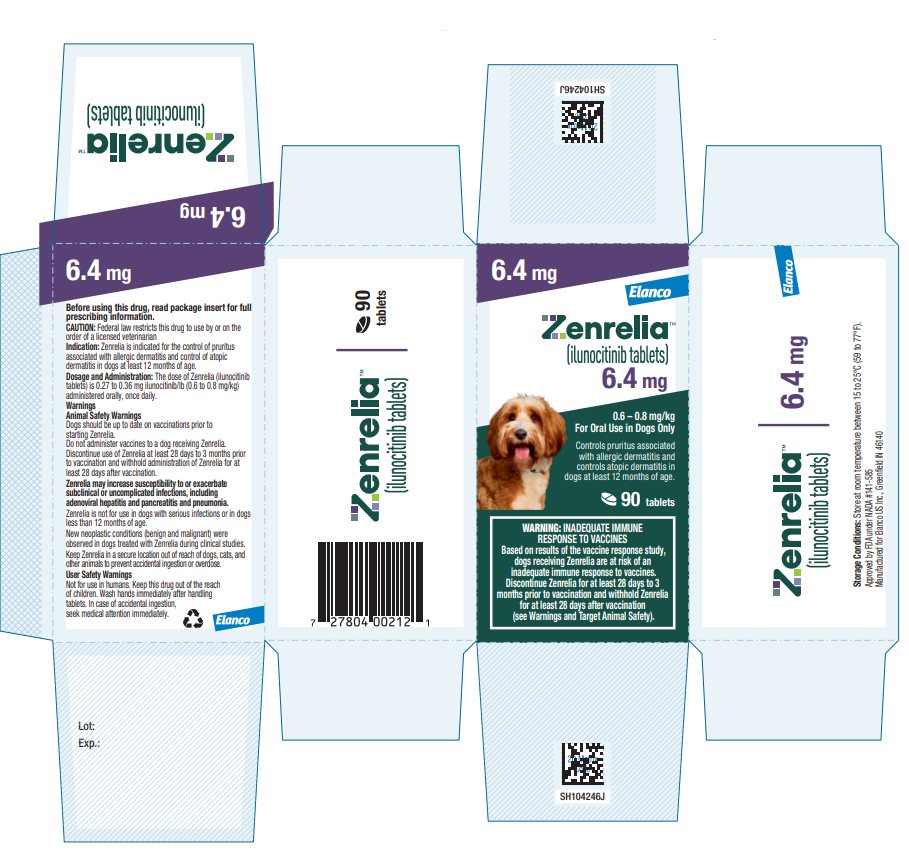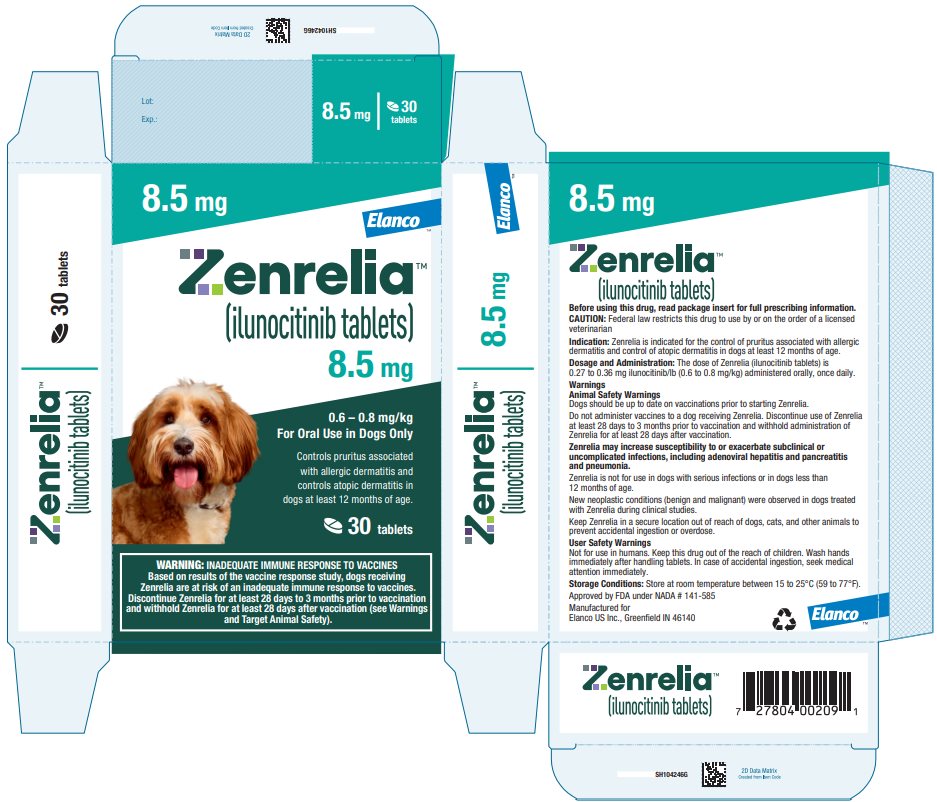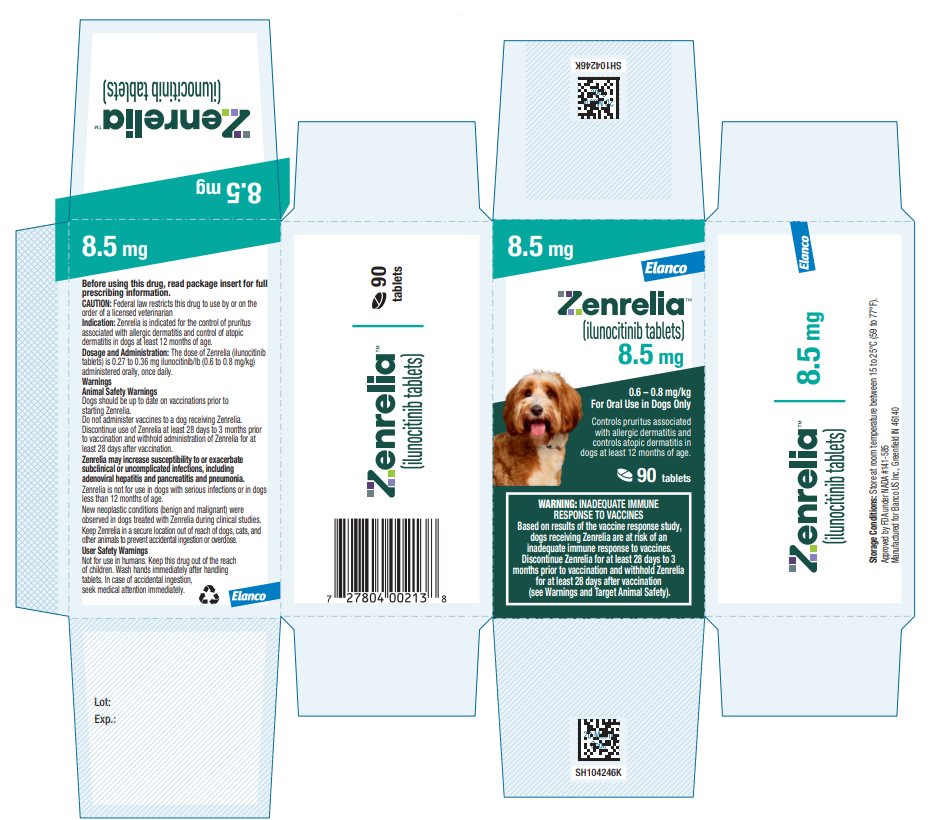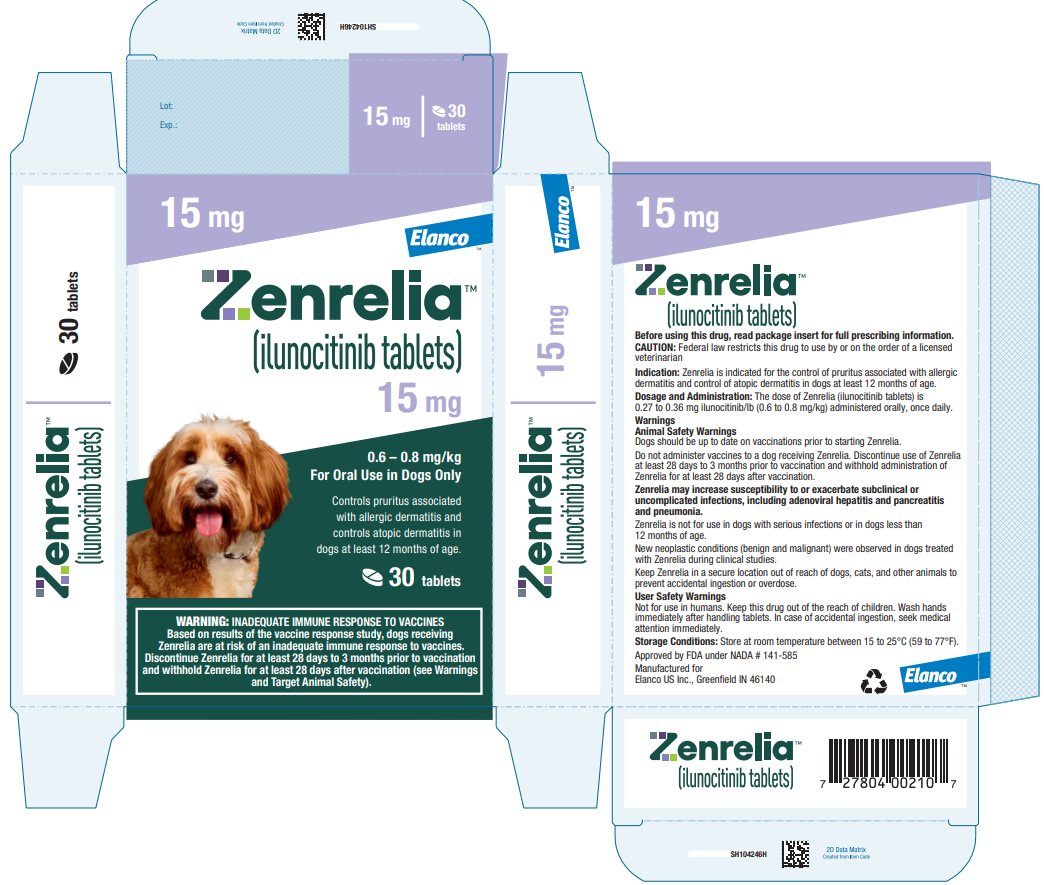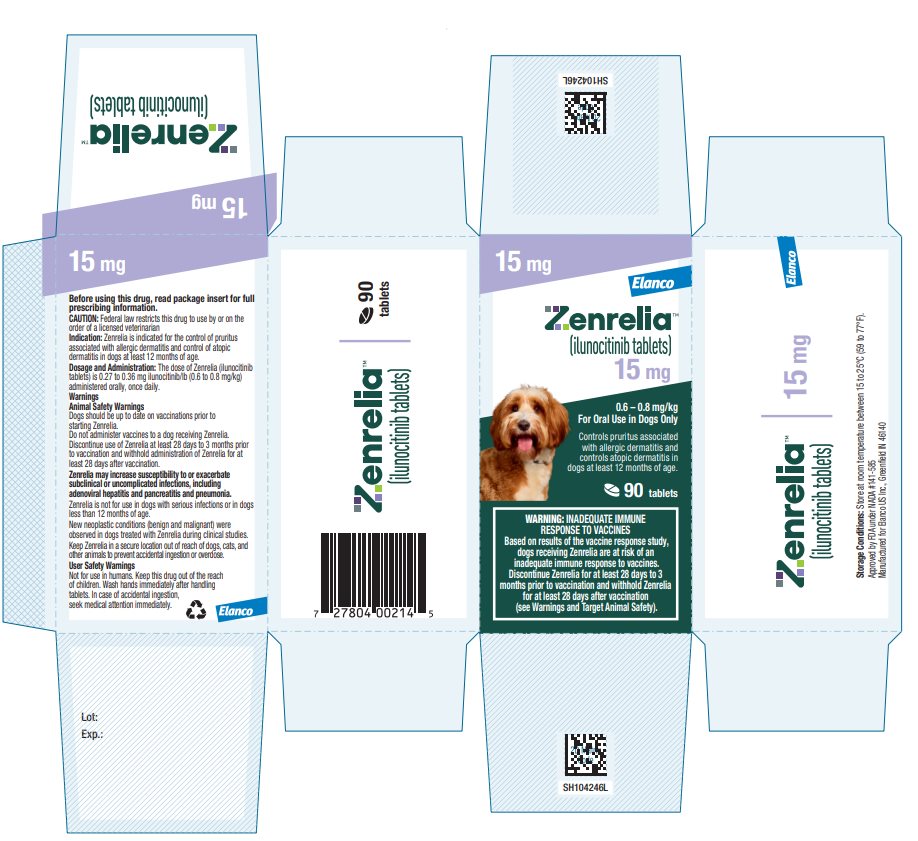 DRUG LABEL: Zenrelia
NDC: 58198-5536 | Form: TABLET
Manufacturer: Elanco US Inc.
Category: animal | Type: PRESCRIPTION ANIMAL DRUG LABEL
Date: 20250923

ACTIVE INGREDIENTS: ILUNOCITINIB 4.8 mg/1 1

Zenrelia™

(ilunocitinib tablets)

Immunomodulator
For oral use in dogs only

CAUTION: Federal law restricts this drug to use by or on the order of a licensed veterinarian.

WARNING: INADEQUATE IMMUNE RESPONSE TO VACCINES

Based on results of the vaccine response study, dogs receiving Zenrelia are at risk of an inadequate immune response to vaccines. Discontinue Zenrelia for at least 28 days to 3 months prior to vaccination and withhold Zenrelia for at least 28 days after vaccination (see Warnings and Target Animal Safety).

DESCRIPTION

Zenrelia is a synthetic Janus kinase (JAK) inhibitor. Zenrelia is a member of the pyrimidines class of JAK inhibitors and its chemical name is 2-[1-cyclopropylsulfonyl-3-[4-(7H-pyrrolo[2,3-d] pyrimidin-4-yl)pyrazol-1-yl]azetidin-3-yl]acetonitrile.

INDICATIONS

Zenrelia is indicated for control of pruritus associated with allergic dermatitis and control of atopic dermatitis in dogs at least 12 months of age.

DOSAGE AND ADMINISTRATION

The dose of Zenrelia (ilunocitinib tablets) is 0.27 to 0.36 mg ilunocitinib/lb (0.6 to 0.8 mg ilunocitinib/kg) body weight, administered orally, once daily, with or without food.

Dosing Chart

Weight Range (in lb) | Weight Range (in kg) | Number of Tablets to be Administered
Weight Range (in lb) | Weight Range (in kg) | 4.8 mg tablets | 6.4 mg tablets | 8.5 mg tablets | 15 mg tablets
6.6 – 8.8 | 3.0 - 4.0 | 0.5
8.9 – 11.8 | 4.1 – 5.3 |  | 0.5
11.9 – 14.3 | 5.4 – 6.5 |  |  | 0.5
14.4 – 17.7 | 6.6 – 8.0 | 1
17.8 – 23.6 | 8.1 – 10.6 |  | 1
23.7 – 31.1 | 10.7 – 14.1 |  |  | 1
31.2 – 35.4 | 14.2 – 16.0 |  | 1.5
35.5 – 43.1 | 16.1 – 19.5 |  |  | 1.5
43.2 – 55.0 | 19.6 – 24.9 |  |  |  | 1
55.1 – 62.5 | 25.0 – 28.3 |  |  | 2
62.6 – 83.3 | 28.4 – 37.4 |  |  |  | 1.5
83.4 – 110.0 | 37.5 – 49.9 |  |  |  | 2
110.1 – 137.5 | 50.0 – 62.4 |  |  |  | 2.5
137.6 – 166.0 | 62.5 – 74.9 |  |  |  | 3
≥ 166.1 | ≥ 75 | Administer the appropriate combination of tablet strengths

WARNINGS

User Safety Warnings

Not for use in humans. Keep this drug out of the reach of children. Wash hands immediately after handling tablets. In case of accidental ingestion, seek medical attention immediately.

Animal Safety Warnings

Due to the risk of infections, dogs should be up to date on vaccinations prior to starting Zenrelia (see Target Animal Safety).

Due to the risk of an inadequate immune response to vaccines, do not administer vaccines to a dog receiving Zenrelia. Discontinue Zenrelia for at least 28 days to 3 months prior to vaccination and withhold Zenrelia for at least 28 days after vaccination (see Target Animal Safety).

Dogs should be monitored for the development of infections because Zenrelia may increase susceptibility to infections, including adenoviral hepatitis and pancreatitis, demodicosis, interdigital furunculosis, coccidiosis, and pneumonia, and exacerbation of subclinical or uncomplicated infections (see Target Animal Safety and Adverse Reactions).

Zenrelia is not for use in dogs with serious infections.

Zenrelia may cause a progressive or persistently decreased hematocrit, hemoglobin, and/or red blood cell count without a corresponding increase in absolute reticulocyte count (see Target Animal Safety).

New neoplastic conditions (benign and malignant) were observed in dogs treated with Zenrelia during clinical studies (see Adverse Reactions).

Consider the risks and benefits of treatment prior to initiating Zenrelia in dogs with a history of recurrent serious infections or recurrent demodicosis or neoplasia (see Adverse Reactions and Target Animal Safety).

Zenrelia modulates the immune system.

Zenrelia is not for use in dogs less than 12 months of age (see Target Animal Safety).

Keep Zenrelia in a secure location out of reach of dogs, cats, and other animals to prevent accidental ingestion or overdose.

PRECAUTIONS

The safe use of Zenrelia has not been evaluated in breeding, pregnant, or lactating dogs.

Decreased prostate gland weights in intact male dogs were observed in a laboratory safety study (see Target Animal Safety).

The safe use of Zenrelia has not been evaluated in combination with glucocorticoids, cyclosporine, or other systemic immunosuppressive agents.

ADVERSE REACTIONS

Control of Atopic Dermatitis

In a masked field study assessing effectiveness and safety of Zenrelia for the control of atopic dermatitis in dogs, 181 Zenrelia-treated dogs and 87 placebo-treated dogs diagnosed with atopic dermatitis were evaluated for safety up to 112 days. By Day 112, 66.7% of placebo-treated dogs and 22.1% of Zenrelia-treated dogs exited the study. Adverse reactions seen during the field study are summarized in Table 1 below.

Table 1. Adverse Reactions through Day 112

Adverse Reaction | Zenrelia N = 181 Number of Dogs (%) | Placebo N = 87 Number of Dogs (%)
Vomiting or nausea | 40 (22.1 %) | 14 (16.1 %)
Diarrhea | 36 (19.9 %) | 9 (10.3 %)
Lethargy | 22 (12.2 %) | 9 (10.3 %)
Otitis externa | 19 (10.5 %) | 20 (23.0 %)
Anorexia | 17 (9.4 %) | 7 (8.0 %)
Dermal growth (e.g., cyst, papilloma) | 16 (8.8 %) | 4 (4.6 %)
Epiphora or ocular discharge | 14 (7.7 %) | 1 (1.1 %)
Coughing or wheezing, including respiratory infections | 12 (6.6 %) | 2 (2.3 %)
Bacterial skin infection | 10 (5.5 %) | 9 (10.3 %)
Elevated liver enzyme(s) | 10 (5.5 %) | 2 (2.3 %)
Urinary tract infection | 10 (5.5 %) | 2 (2.3 %)
Upset stomach, including flatulence and abdominal pain | 10 (5.5 %) | 0
Leukopenia | 9 (4.9 %) | 1 (1.1 %)
Sneezing | 8 (4.4 %) | 1 (1.1 %)
Lipoma | 7 (3.9 %) | 1 (1.1 %)
Weight gain | 7 (3.9 %) | 0
Increased water intake | 4 (2.2 %) | 2 (2.3 %)
Gingivitis (occurrence or worsening) | 4 (2.2 %) | 0
Blood in stool | 4 (2.2 %) | 0
Elevated total bilirubin | 4 (2.2 %) | 0
Elevated triglyceride | 4 (2.2 %) | 0
Histiocytoma | 3 (1.7 %) | 0
Increased appetite | 3 (1.7 %) | 0
Fungal skin infection | 3 (1.7 %) | 2 (2.3 %)
Weight loss | 2 (1.1 %) | 1 (1.1 %)
Metastatic neoplasia (i.e., hemangiosarcoma) | 1 (0.6 %) | 0
Systemic fungal infection | 1 (0.6 %) | 0
Mast cell tumor | 1 (0.6 %) | 0
N = number of dogs

Abnormal hematology results likely related to Zenrelia treatment included thrombocytopenia, leukopenia, neutropenia, lymphopenia, eosinopenia, monocytopenia, and decreased red blood cell count.

Abnormal serum chemistry results likely related to Zenrelia treatment included increased hepatobiliary parameters (alanine transaminase, aspartate aminotransferase, alkaline phosphatase, gamma-glutamyl transferase, and total bilirubin), increased blood urea nitrogen (concurrently with an increase in creatinine for one dog), hypertriglyceridemia, hypercholesterolemia, hypoalbuminemia (without a concurrent hyperglobulinemia), and hypoglobulinemia (with or without a decrease in total protein).

Twelve Zenrelia-treated dogs withdrew from the study early due to an adverse reaction, nine of which were considered likely related to Zenrelia treatment. These reactions included repeated episodes of vomiting, leukopenia, neutropenia, worsening of pre-existing lymphocytosis, enlargement of a non-resolving histiocytoma, eyelid mass with bacterial blepharitis, otitis interna with vestibular disease, urinary tract infection, and upper respiratory infection. Five placebo dogs withdrew from the study early due to an adverse reaction (i.e., lethargy, worsening of pre-existing lymphocytosis, occurrence of nystagmus, skin infection, and teat infection).

One Zenrelia-treated dog was diagnosed with splenic and liver masses on Day 112. Histopathologic diagnosis after euthanasia one month later confirmed metastatic splenic and hepatic hemangiosarcoma. Another Zenrelia-treated dog experienced traumatic tendonitis and a puncture wound four days prior to study completion, which progressed to a serious infection. The owner elected amputation after study completion. A third Zenrelia-treated dog experienced a moderate neutropenia on Day 28 associated with a pre-existing subclinical urinary tract infection (UTI) that had progressed into a clinical UTI. The neutrophil count normalized seven days later while still receiving Zenrelia, prior to exiting the study to receive antibiotics.

Control of Pruritus Associated with Allergic Dermatitis

In a masked field study assessing effectiveness and safety of Zenrelia for the control of pruritus associated with allergic dermatitis in dogs, 206 Zenrelia-treated dogs and 100 placebo-treated dogs diagnosed with allergic dermatitis were evaluated for safety up to 112 days. By Day 112, 84% of placebo-treated dogs and 49.5% of Zenrelia-treated dogs exited the study. Adverse reactions seen during the field study are summarized in Table 2 below.

Table 2. Adverse Reactions through Day 112

Adverse Reaction | Zenrelia N = 206 Number of Dogs (%) | Placebo N = 100 Number of Dogs (%)
Vomiting or nausea | 32 (15.5%) | 11 (11.0 %)
Diarrhea | 26 (12.2 %) | 5 (5.0 %)
Lethargy | 25 (12.1 %) | 7 (7.0 %)
Urinary tract infection | 13 (6.3 %) | 2 (2.0 %)
Anorexia | 10 (4.9 %) | 3 (3.0 %)
Coughing, wheezing, or difficulty breathing | 9 (4.4 %) | 0
Elevated liver enzyme(s) | 8 (3.9 %) | 0
Otitis externa | 8 (3.9 %) | 5 (5.0 %)
Increased water intake | 7 (3.4 %) | 2 (2.0 %)
Upset stomach, including flatulence, retching, and abdominal pain | 5 (2.4 %) | 4 (4.0 %)
Ocular discharge | 5 (2.4 %) | 1 (1.0 %)
Elevated triglyceride | 5 (2.4 %) | 0
Dermal or subcutaneous growth (e.g., cyst, nodule) | 3 (1.5 %) | 2 (2.0 %)
Sneezing | 3 (1.5 %) | 0
Blood in stool | 3 (1.5 %) | 0
Increased urination | 3 (1.5 %) | 0
Bacterial skin infection | 2 (1.0 %) | 4 (4.0 %)
Weight gain | 2 (1.0 %) | 0
Neurological disorder (e.g., tremors, ataxia) | 2 (1.0 %) | 0
Increased appetite | 1 (0.5 %) | 0
Fungal skin infection | 1 (0.5 %) | 0
Fever | 1 (0.5 %) | 0
Hematuria (without urinary tract infection) | 1 (0.5 %) | 0
N = number of dogs

Abnormal hematology results likely related to Zenrelia treatment included thrombocytosis, leukopenia, neutropenia, eosinopenia, and monocytopenia.

Abnormal serum chemistry results likely related to Zenrelia treatment included increased hepatobiliary parameters (alanine transaminase, aspartate aminotransferase, alkaline phosphatase, gamma-glutamyl transferase, and total bilirubin), increased blood urea nitrogen, increased creatinine, hypertriglyceridemia, hypercholesterolemia, hypoproteinemia, and hypoglobulinemia (with or without a decrease in total protein).

Seven Zenrelia-treated dogs withdrew from the study early due to an adverse reaction, four of which were considered likely related to Zenrelia treatment. These reactions included vomiting, lethargy, soft stool, neutropenia, increased liver enzymes, fever, abdominal discomfort, coughing, and wheezing. Four placebo treated dogs also withdrew from the study early due to an adverse reaction (i.e., splenic hemangiosarcoma, restlessness, abdominal pain, lethargy, and vomiting).

CONTACT INFORMATION

To report suspected adverse events, for technical assistance, or to obtain a copy of the Safety Data Sheet (SDS), contact Elanco US Inc at 1-888-545-5973.

For additional information about reporting adverse drug experiences for animal drugs, contact FDA at 1-888-FDA-VETS or http://www.fda.gov/reportanimalae.

CLINICAL PHARMACOLOGY

Mechanism of Action

Ilunocitinib is a non-selective JAK inhibitor which inhibits the function of a variety of pruritogenic, pro-inflammatory and allergy related cytokines that are dependent upon JAK enzymes. Ilunocitinib has a high potency for JAK1, JAK2, and tyrosine kinase 2 (TYK2) inhibition. Ilunocitinib is not a corticosteroid or an antihistamine.

Pharmacokinetics

Ilunocitinib is rapidly and well absorbed and excreted via the biliary/fecal route after oral administration in dogs. Following a single oral or intravenous administration of ilunocitinib at 0.8 mg/kg, the oral bioavailability based on area under the curve from the time of dosing to the last quantifiable plasma concentration (AUClast) was 80% in the fed state and 60% in the fasted state. The systemic clearance following intravenous administration was 399 mL/hour(h)/kg with a terminal half-life of 3.6 h. The volume of distribution was 1390 mL/kg (n=8). The maximum plasma concentration (Cmax) and AUClast were 120% and 45% higher, respectively, in the fed state as compared to the fasted state (n=16).

In a laboratory margin of safety study, healthy adult dogs (see Target Animal Safety) received daily oral administration of Zenrelia at 0.8 mg/kg, 1.6 mg/kg, 2.4 mg/kg, or 4.0 mg/kg for 182 consecutive days. Dogs were dosed in the fed state, the prandial state of maximum bioavailability. At 0.8 mg/kg, the ilunocitinib mean (coefficient of variation %) Cmax was 310 ng/mL (20.6%) with a median time to Cmax of 2 h (range 1 – 2 h), and the AUClast and half-life were 1360 h*ng/mL (25.1%) and 3.3 h (11.9%), respectively. Minimal accumulation was observed between Days 1 and 182 with geometric mean accumulation ratios for Cmax and AUClast between 1.1 and 1.6. After the first dose, Cmax increased in a linear but less than proportional manner where a 5-fold increase in dose resulted in a 3.4-fold (90% confidence limit: 2.9 – 4.0) increase in Cmax. There was a non-linear relationship between dose and AUClast where a 5-fold increase in dose resulted in a 4.2-fold (90% confidence limit: 3.4 – 5.1) increase in AUClast. Pharmacokinetic parameters are presented as geometric means.

EFFECTIVENESS

Control of Atopic Dermatitis:

A masked, placebo-controlled field study was conducted at 25 veterinary clinics in the US and Canada, enrolling 268 client-owned dogs diagnosed with atopic dermatitis and having at least moderate pruritus and mild skin lesions. Dogs were randomized to once daily treatment with Zenrelia at 0.6 – 0.8 mg/kg or placebo, at a ratio of 2:1 respectively. Other medications that could affect the evaluation of effectiveness were not allowed during the study, such as corticosteroids, antihistamines, and cyclosporine. Treatment success for each dog was defined as a ≥ 50% reduction from baseline in owner-assessed pruritus scores on the Pruritus Visual Analog Scale (PVAS) or a ≥ 50% reduction from baseline in veterinarian-assessed skin lesion scores on the Canine Atopic Dermatitis Extent and Severity Index version 4 (CADESI-4) on Day 28. The proportion of dogs in the Zenrelia group that were treatment successes was greater than and significantly different from the placebo group on Day 28 (Table 3, below).

Table 3. Estimated Proportion of Dogs Achieving Treatment Success

Treatment Group | Estimated Proportion of Success*
Zenrelia (N = 172) | 0.83
Placebo (N = 77) | 0.31†
* Based on back-transformed least squares means.
† Placebo vs. Zenrelia p < 0.001
N = Number of dogs

The Zenrelia group had a higher proportion of dogs with a ≥ 50% reduction from baseline in both owner-assessed PVAS and veterinarian-assessed CADESI-4 scores, compared to placebo, at all time points. The mean owner-assessed PVAS and veterinarian-assessed CADESI-4 scores were also lower for the Zenrelia group compared to the placebo group at all time points.

Control of Pruritus Associated with Allergic Dermatitis

A masked, placebo-controlled field study was conducted at 15 veterinary clinics in the US, enrolling 306 client-owned dogs diagnosed with allergic dermatitis and having at least moderate pruritus. The allergic dermatitis was attributed to one or more of the following conditions: atopic dermatitis, contact dermatitis, flea allergy dermatitis, food hypersensitivity, or other. Dogs were randomized to once daily treatment with Zenrelia at 0.6 – 0.8 mg/kg or placebo, at a ratio of 2:1 respectively. Other medications that could affect the evaluation of effectiveness were not allowed during the study, such as corticosteroids, antihistamines, and cyclosporine. Treatment success for each dog was defined as a ≥ 50% reduction from baseline in owner-assessed pruritus scores on the Pruritus Visual Analog Scale (PVAS) on at least 5 out of the first 7 days of treatment. The proportion of dogs in the Zenrelia group that were treatment successes was greater than and significantly different compared to the placebo group on Day 7 (Table 4, below).

Table 4. Estimated Proportion of Dogs Achieving Treatment Success

Treatment Group | Estimated Proportion of Success*
Zenrelia (N = 193) | 0.25
Placebo (N = 91) | 0.08†
* Based on back-transformed least squares means.
† Placebo vs. Zenrelia p = 0.006
N = number of dogs

The Zenrelia group had a higher proportion of dogs with a ≥ 50% reduction from baseline in owner-assessed PVAS, compared to placebo, on Days 2 through 7.

After Day 1, mean owner-assessed PVAS scores were lower in the Zenrelia group (Figure 1, below).

Figure 1. Mean owner-assessed PVAS Scores by Treatment for Days 0-7

Veterinarians used a dermatitis visual analog scale (DVAS) to assess each dog’s dermatitis. Veterinarian-assessed DVAS scores were lower for the Zenrelia group compared to the placebo group at all time points through Day 28.

TARGET ANIMAL SAFETY

Margin of Safety Study:

Zenrelia was administered to 40 (8 dogs per group) healthy, 11 to 12-month-old, fed Beagle dogs, once daily at 0X, 1X, 2X, 3X and 5X the maximum exposure dose of 0.8 mg/kg for 6 months. Control dogs were sham-dosed. Zenrelia-related clinical observations included a dose-dependent increase in the frequency and severity of interdigital furunculosis (cysts), with or without discharge on one or more paws, swollen and/or scabbing paws, and paw skin thickening and/or discoloration. Zenrelia-related hemogram findings included a dose-dependent minimal to moderate decrease in hematocrit (HCT), hemoglobin (HGB), and red blood cell (RBC) count without a corresponding increase in absolute reticulocyte count. Other Zenrelia-related findings included a minimal to mild decrease in mean corpuscular hemoglobin (MCH), mean corpuscular hemoglobin concentrations (MCHC), and eosinophil counts. Abnormal clinical pathology observations considered secondary to the interdigital furunculosis, included minimal to moderate increases in fibrinogen concentrations, total protein, C-reactive protein, and globulins, and decreases in albumin, albumin/globulin ratio and calcium levels. There were no Zenrelia-related effects on lymphocytes, monocytes, and basophils. Two dogs in the 5X group had minimally lower myeloid:erythroid ratios consistent with a physiological bone marrow response to the lower red blood cell mass despite no apparent effect on absolute reticulocytes. Zenrelia-related pathology changes included decreased prostate gland weights in the 5X group males and interdigital papillomas and/or dermatitis/furunculosis, predominantly in the 5X group. One dog in the 5X group had enlarged and mildly reactive draining lymph nodes associated with interdigital furunculosis. One dog in the 3X group had a papilloma on each paw with fragments of Demodex canis, and a follicular cyst within the markedly inflamed dermis.

Vaccine Response Study:

Zenrelia was administered to 16 (8 dogs per group) healthy, 10-month-old, vaccine naïve Beagle dogs, once daily at 0 and 3X the maximum exposure dose of 0.8 mg/kg for 89 days. Control dogs were placebo dosed. An 84-day recovery period followed in which no drug was administered. Dogs were administered a multivalent modified live virus (MLV) vaccine, including canine adenovirus type-2 (CAV-2), canine parvovirus (CPV), and canine distemper virus (CDV), on Days 28 and 60 and a killed rabies virus (RV) vaccine on Day 60.

The primary endpoint was achievement on Day 88 of predefined serum titer thresholds considered adequate for protective immunity. Serum titers were also evaluated 27 days (RV only) and 83 days after discontinuing drug administration (Days 116 and 172, respectively).

On Day 52, one dog administered Zenrelia was euthanized due to lethargy, depression, poor body condition, and weakness. Necropsy revealed findings consistent with a colonic intussusception, potentially related to a clinical Cystoisospora canis infection secondary to Zenrelia-induced immunosuppression.

On Day 54, another dog administered Zenrelia was euthanized due to lethargy, depression, poor body condition, and weakness. Histopathology evaluation revealed marked necrotizing hepatitis and pancreatitis and evidence of systemic endotoxemia. Prominent intranuclear inclusion bodies were found in the liver and pancreas, consistent with adenoviral infection. Polymerase chain reaction (PCR) analysis and DNA sequencing conducted post-mortem on preserved liver tissues from both euthanized dogs were positive for the presence of canine adenovirus type 1 (CAV-1) and canine adenovirus type 2 (CAV-2) DNA. Although the presence of live virus could not be confirmed, the presence of another adenovirus suggests that the fatal adenoviral hepatitis and pancreatitis was not vaccine induced and may have been due to a natural adenoviral infection, such as infectious canine hepatitis.

Clinical signs observed in Zenrelia-treated dogs included poor body condition, pale mucous membranes, lethargy, diarrhea, vomiting, weight loss, decreased appetite, and depression likely due to a clinical C. canis infection secondary to Zenrelia-induced immunosuppression in seven of the eight dogs. No dogs in the control group were diagnosed with a C. canis infection. One dog in the control group had diarrhea. Zenrelia-related clinical observations also included interdigital cysts, lameness, and thickening and crusting of the ear margins. Clinical pathology findings in Zenrelia-treated dogs included decreases in hematocrit, hemoglobin, and red blood cell counts with a corresponding increase in absolute reticulocyte count, and decreases in total serum protein, albumin, and globulins, likely due to the C. canis infection.

On Day 88, all eight control dogs demonstrated an adequate immune response to CAV-2, CPV, CDV, and RV vaccination and all six remaining dogs receiving Zenrelia demonstrated an adequate immune response to CAV-2 and CPV vaccination. Four (of six) Zenrelia-treated dogs failed to demonstrate an adequate immune response to RV vaccination, and one (of six) Zenrelia-treated dogs failed to demonstrate an adequate immune response to CDV vaccination on Day 88.

During the recovery period, on Day 116 (27 days after discontinuing treatment), one (of eight) control dogs and one (of six) Zenrelia-treated dogs failed to demonstrate an adequate immune response to RV vaccination. On Day 172 (83 days after discontinuing treatment), all eight control dogs demonstrated an adequate immune response to CAV-2, CPV, and CDV vaccination, all six remaining Zenrelia-treated dogs demonstrated an adequate immune response to CAV-2 and CPV vaccination, one (of six) Zenrelia-treated dogs failed to demonstrate an adequate immune response to CDV vaccination, and one (of eight) control dogs and three (of six) Zenrelia-treated dogs failed to demonstrate an adequate immune response to RV vaccination.

Potential recovery from drug-induced immunosuppression 27 days after discontinuing Zenrelia is evidenced by the observed adequate immune response to RV vaccination on Day 116 in three of the four dogs in the Zenrelia group that failed to achieve an adequate RV titer while receiving Zenrelia on Day 88. However, one of these four dogs did not achieve adequate RV titers after Zenrelia was discontinued for 83 days. A 3-month washout period prior to vaccination is supported by the 2024 World Small Animal Veterinary Association and 2023 Center for Disease Control and Prevention vaccination guidelines. The 28-day time period to withhold Zenrelia after vaccination is based on published and unpublished data evaluating the duration of MLV vaccine virus shedding.

Pilot Margin of Safety Study:

A non-final formulation of ilunocitinib (oral suspension) was administered via gavage to 32 (8 dogs per group) healthy, 9-month-old, Beagle dogs, once daily at 0X, 1X, 3X, and 4.5X the maximum exposure dose of 0.8 mg/kg through Day 64. Due to serious adverse reactions in the 3X and 4.5X groups, on Day 65, the 4.5X group was decreased to 2X through Day 185. Control dogs were sham dosed. One dog in the 4.5X group and two dogs in the 3X group were prematurely euthanized (on Days 52, 57, and 134, respectively) due to an acute onset of lethargy, labored breathing, fever, tremors, and pale gums, starting within four hours of dosing via oral gavage. Microscopic pathology findings in the three dogs included necrotizing hemorrhagic pneumonia, considered secondary to ilunocitinib-induced immunosuppression and gavage administration. Two of these three dogs developed severe leukopenia and neutropenia and one dog had severe weight loss in the two weeks prior to euthanasia. Twelve dogs administered ilunocitinib, including the three dogs prematurely euthanized, had a decrease in at least one RBC parameter (HCT, HGB, or RBC count), without a corresponding increase in absolute reticulocyte count, at one or more timepoints during the study. Additional ilunocitinib-related microscopic pathology changes included minimal to mild increased erythropoiesis and pigment in the spleen, minimal to mild pigmented macrophages in the liver, and minimal adipocyte accumulation in the bone marrow.

STORAGE CONDITIONS

Store at room temperature between 15 to 25°C (59 to 77°F), excursions permitted between 5 to 40°C (41 to 104°F).

HOW SUPPLIED

Zenrelia (ilunocitinib tablets) is available in scored tablets in four strengths: 4.8 mg, 6.4 mg, 8.5 mg, and 15 mg. Each tablet strength is available in 10 and 30 count blister packages and 90 count bottles.

Manufactured for Elanco US Inc. Greenfield, IN 46140

Approved by FDA under NADA # 141-585

Zenrelia, Elanco and the diagonal bar logo are trademarks of Elanco or its affiliates.
© 2025 Elanco or its affiliates

July 2025
PA104246X

Elanco™

Principal Display Panel - Zenrelia 4.8 mg

Elanco™

Zenrelia™

(ilunocitinib tablets)

4.8 mg

0.6 – 0.8 mg/kg
For Oral Use in Dogs Only

Controls pruritus associated
with allergic dermatitis and
controls atopic dermatitis in
dogs at least 12 months of age.

30 tablets

Elanco

Zenrelia™

(ilunocitinib tablets)

4.8 mg

0.6 – 0.8 mg/kg
For Oral Use in Dogs Only

Controls pruritus associated
with allergic dermatitis and
controls atopic dermatitis in
dogs at least 12 months of age.

90 tablets

Principal Display Panel - Zenrelia 6.4 mg

Elanco™

Zenrelia™

(ilunocitinib tablets)

6.4 mg

0.6 – 0.8 mg/kg
For Oral Use in Dogs Only

Controls pruritus associated
with allergic dermatitis and
controls atopic dermatitis in
dogs at least 12 months of age.

30 tablets

Elanco

Zenrelia™

(ilunocitinib tablets)

6.4 mg

0.6 – 0.8 mg/kg
For Oral Use in Dogs Only

Controls pruritus associated
with allergic dermatitis and
controls atopic dermatitis in
dogs at least 12 months of age.

90 tablets

Principal Display Panel - Zenrelia 8.5 mg

Elanco™

Zenrelia™

(ilunocitinib tablets)

8.5 mg

0.6 – 0.8 mg/kg
For Oral Use in Dogs Only

Controls pruritus associated
with allergic dermatitis and
controls atopic dermatitis in
dogs at least 12 months of age.

30 tablets

Elanco

Zenrelia™

(ilunocitinib tablets)

8.5 mg

0.6 – 0.8 mg/kg
For Oral Use in Dogs Only

Controls pruritus associated
with allergic dermatitis and
controls atopic dermatitis in
dogs at least 12 months of age.

90 tablets

Principal Display Panel - Zenrelia 15 mg

Elanco™

Zenrelia™

(ilunocitinib tablets)

15 mg

0.6 – 0.8 mg/kg
For Oral Use in Dogs Only

Controls pruritus associated
with allergic dermatitis and
controls atopic dermatitis in
dogs at least 12 months of age.

30 tablets

Elanco

Zenrelia™

(ilunocitinib tablets)

15 mg

0.6 – 0.8 mg/kg
For Oral Use in Dogs Only

Controls pruritus associated
with allergic dermatitis and
controls atopic dermatitis in
dogs at least 12 months of age.

90 tablets